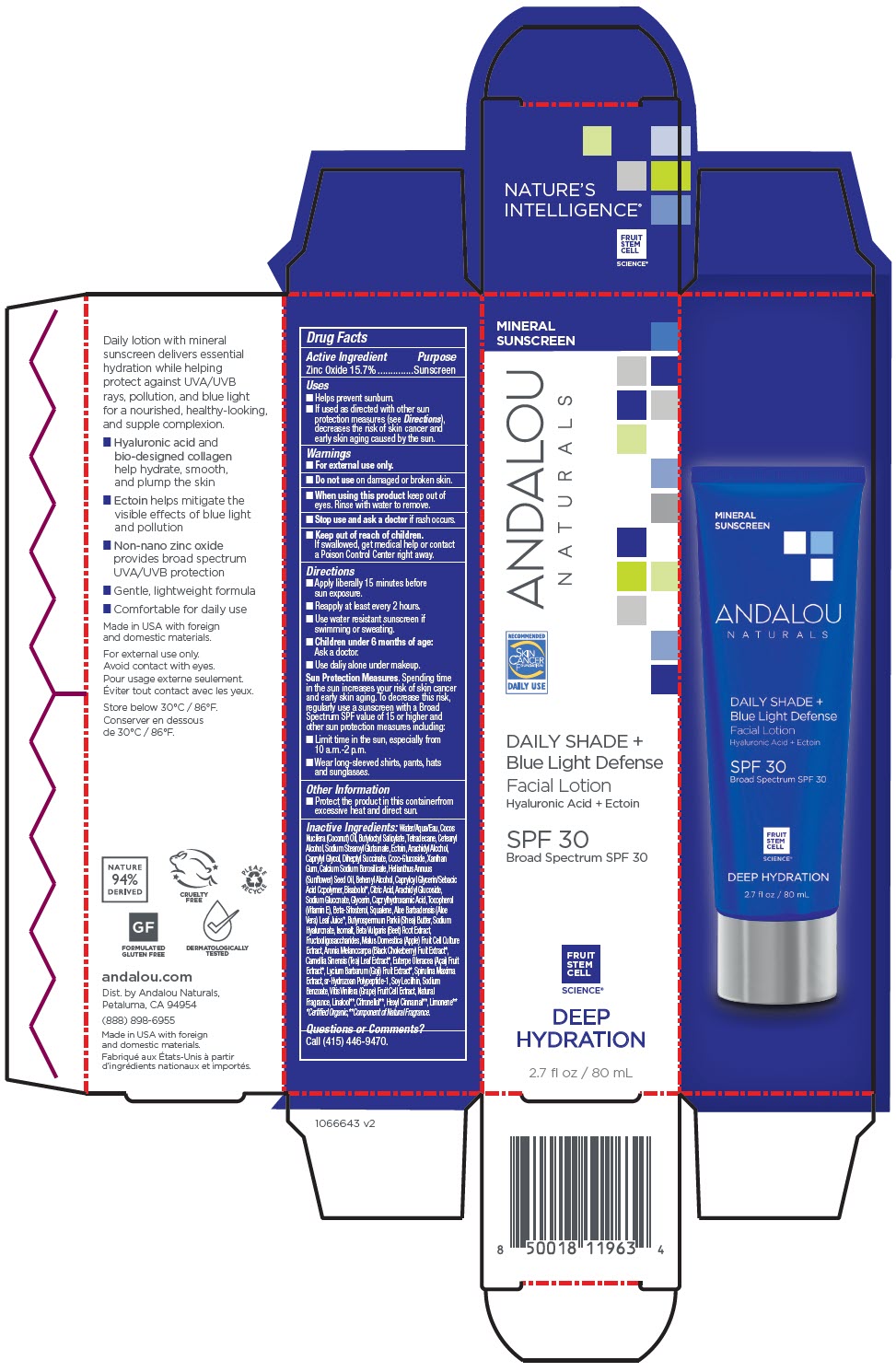 DRUG LABEL: ANDALOU NATURALS DEEP HYDRATION DAILY SHADE BLUE LIGHT DEFENSE FACIAL SPF 30
NDC: 55560-2201 | Form: LOTION
Manufacturer: Andalou naturals
Category: otc | Type: HUMAN OTC DRUG LABEL
Date: 20250609

ACTIVE INGREDIENTS: ZINC OXIDE 157 mg/1 mL
INACTIVE INGREDIENTS: WATER; COCONUT OIL; BUTYLOCTYL SALICYLATE; TETRADECANE; CETOSTEARYL ALCOHOL; SODIUM STEAROYL GLUTAMATE; ECTOINE; ARACHIDYL ALCOHOL; CAPRYLYL GLYCOL; DIHEPTYL SUCCINATE; COCO-GLUCOSIDE; XANTHAN GUM; CALCIUM SODIUM BOROSILICATE; SUNFLOWER OIL; DOCOSANOL; CAPRYLOYL GLYCERIN/SEBACIC ACID COPOLYMER (2000 MPA.S); LEVOMENOL; ANHYDROUS CITRIC ACID; ARACHIDYL GLUCOSIDE; SODIUM GLUCONATE; GLYCERIN; CAPRYLHYDROXAMIC ACID; TOCOPHEROL; .BETA.-SITOSTEROL; SQUALENE; ALOE VERA LEAF; SHEA BUTTER; HYALURONATE SODIUM; ISOMALT; BEET; SACCHARUM OFFICINARUM STEM FRUCTOOLIGOSACCHARIDES; APPLE; ARONIA MELANOCARPA FRUIT JUICE; TEA LEAF; ACAI; LYCIUM BARBARUM FRUIT; ARTHROSPIRA MAXIMA; PODOCORYNA CARNEA FIBRILLAR COLLAGEN; SOYBEAN LECITHIN; SODIUM BENZOATE; VITIS VINIFERA HIGH TANNIN CULTIVAR FRUIT CELL LYSATE

ANDALOU NATURALS DEEP HYDRATION DAILY SHADE BLUE LIGHT DEFENSE FACIAL SPF 30

Drug Facts

Active Ingredient

Zinc Oxide 15.7%

Purpose

Sunscreen

Uses

- Helps prevent sunburn.
- If used as directed with other sun protection measures (see Directions), decreases the risk of skin cancer and early skin aging caused by the sun.

Warnings

- For external use only.

- Do not use on damaged or broken skin.

- When using this product keep out of eyes. Rinse with water to remove.

- Stop use and ask a doctor if rash occurs.

- Keep out of reach of children.

If swallowed, get medical help or contact a Poison Control Center right away.

Directions

- Apply liberally 15 minutes before sun exposure.
- Reapply at least every 2 hours.
- Use water resistant sunscreen if swimming or sweating.
- Children under 6 months of age: Ask a doctor.
- Use daily or alone under makeup.

Sun Protection Measures. Spending time in the sun increases your risk of skin cancer and early skin aging. To decrease this risk, regularly use a sunscreen with a Broad Spectrum SPF value of 15 or higher and other sun protection measures including:

- Limit time in the sun, especially from 10 a.m.-2 p.m.
- Wear long-sleeved shirts, pants, hats and sunglasses.

Other Information

- Protect the product in this container from excessive heat and direct sun.

Inactive Ingredients

Water/Aqua/Eau, Cocos Nucifera (Coconut) Oil, Butyloctyl Salicylate, Tetradecane, Cetearyl Alcohol, Sodium Stearoyl Glutamate, Ectoin, Arachidyl Alcohol, Caprylyl Glycol, Diheptyl Succinate, Coco-Glucoside, Xanthan Gum, Calcium Sodium Borosilicate, Helianthus Annuus (Sunflower) Seed Oil, Behenyl Alcohol, Capryloyl Glycerin/Sebacic Acid Copolymer, Bisabolol [Certified Organic,] , Citric Acid, Arachidyl Glucoside, Sodium Gluconate, Glycerin, Caprylhydroxamic Acid, Tocopherol (Vitamin E), Beta-Sitosterol, Squalene, Aloe Barbadensis (Aloe Vera) Leaf Juice, Butyrospermum Parkii (Shea) Butter, Sodium Hyaluronate, Isomalt, Beta Vulgaris (Beet) Root Extract, Fructooligosaccharides, Malus Domestica (Apple) Fruit Cell Culture Extract, Aronia Melanocarpa (Black Chokeberry) Fruit Extract, Camellia Sinensis (Tea) Leaf Extract, Euterpe Oleracea (Açai) Fruit Extract, Lycium Barbarum (Goji) Fruit Extract, Spirulina Maxima Extract, sr-Hydrozoan Polypeptide-1, Soy Lecithin, Sodium Benzoate, Vitis Vinifera (Grape) Fruit Cell Extract, Natural Fragrance, Linalool [Component of Natural Fragrance.] , Citronellol , Hexyl Cinnamal , Limonene

Questions or Comments?

Call (415) 446-9470.

Dist. by Andalou Naturals,
Petaluma, CA 94954.

PRINCIPAL DISPLAY PANEL - 80 mL Tube Carton

MINERAL
SUNSCREEN

ANDALOU
NATURALS

RECOMMENDED
Skin
Cancer
Foundation
DAILY USE

DAILY SHADE +
Blue Light Defense
Facial Lotion
Hyaluronic Acid + Ectoin

SPF 30
Broad Spectrum SPF 30

FRUIT
STEM
CELL
SCIENCE®

DEEP
HYDRATION

2.7 fl oz / 80 mL